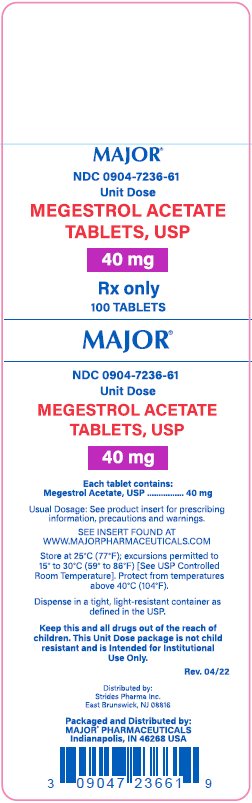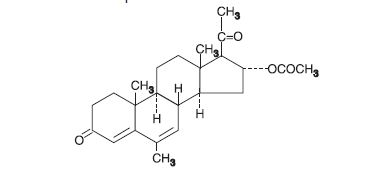 DRUG LABEL: Megestrol Acetate
NDC: 0904-7236 | Form: TABLET
Manufacturer: Major Pharmaceuticals
Category: prescription | Type: HUMAN PRESCRIPTION DRUG LABEL
Date: 20250915

ACTIVE INGREDIENTS: MEGESTROL ACETATE 40 mg/1 1
INACTIVE INGREDIENTS: ACACIA; SILICON DIOXIDE; STARCH, CORN; DIBASIC CALCIUM PHOSPHATE DIHYDRATE; LACTOSE MONOHYDRATE; MAGNESIUM STEARATE

MEGESTROL ACETATE TABLETS, USP

Rx only

DESCRIPTION

Megestrol acetate is a synthetic, antineoplastic and progestational drug. Megestrol acetate is a white, crystalline solid chemically designated as 17(alpha)-(acetyloxy)-6-methylpregna-4,6-diene-3,20-dione. Solubility at 37°C in water is 2 mcg per mL, solubility in plasma is 24 mcg per mL. Its molecular weight is 384.51. The molecular formula is C24H32O4 and the structural formula is represented as follows:

Megestrol acetate is supplied as tablets for oral administration containing 20 mg and 40 mg megestrol acetate.

Megestrol acetate tablets contain the following inactive ingredients: acacia spray dried, colloidal silicon dioxide, corn starch, di-calcium phosphate dihydrate powder, lactose hydrous impalpable, magnesium stearate and pregelatinized starch.

CLINICAL PHARMACOLOGY

While the precise mechanism by which megestrol produces its antineoplastic effects against endometrial carcinoma is unknown at the present time, inhibition of pituitary gonadotropin production and resultant decrease in estrogen secretion may be factors. There is evidence to suggest a local effect as a result of the marked changes brought about by the direct instillation of progestational agents into the endometrial cavity. The antineoplastic action of megestrol acetate on carcinoma of the breast is effected by modifying the action of other steroid hormones and by exerting a direct cytotoxic effect on tumor cells. In metastatic cancer, hormone receptors may be present in some tissues but not others. The receptor mechanism is a cyclic process whereby estrogen produced by the ovaries enters the target cell, forms a complex with cytoplasmic receptor and is transported into the cell nucleus. There it induces gene transcription and leads to the alteration of normal cell functions. Pharmacologic doses of megestrol acetate not only decrease the number of hormone-dependent human breast cancer cells but also are capable of modifying and abolishing the stimulatory effects of estrogen on these cells. It has been suggested that progestins may inhibit in one of two ways: by interfering with either the stability, availability, or turnover of the estrogen receptor complex in its interaction with genes or in conjunction with the progestin receptor complex, by interacting directly with the genome to turn off specific estrogen-responsive genes.

There are several analytical methods used to estimate megestrol acetate plasma levels, including mass fragmentography, gas chromatography (GC), high pressure liquid chromatography (HPLC), and radioimmunoassay. The plasma levels by HPLC assay or radioimmunoassay methods are about one-sixth those obtained by the GC method. The plasma levels are dependent not only on the method used, but also on intestinal and hepatic inactivation of the drug, which may be affected by factors such as intestinal tract motility, intestinal bacteria, antibiotics administered, body weight, diet, and liver function.

Metabolites account for only 5% to 8% of the administered dose and are considered negligible. The major route of drug elimination in humans is the urine. When radiolabeled megestrol acetate was administered to humans in doses of 4 to 90 mg, the urinary excretion within 10 days ranged from 56.5% to 78.4% (mean 66.4%) and fecal excretion ranged from 7.7% to 30.3% (mean 19.8%). The total recovered radioactivity varied between 83.1% and 94.7% (mean 86.2%). Respiratory excretion as labeled carbon dioxide and fat storage may have accounted for at least part of the radioactivity not found in the urine and feces.

In normal male volunteers (n=23) who received 160 mg of megestrol acetate given as a 40 mg q.i.d. regimen, the oral absorption of megestrol acetate appeared to be variable. Plasma levels were assayed by a high pressure liquid chromatographic (HPLC) procedure. Peak drug levels for the first 40 mg dose ranged from 10 to 56 ng/mL (mean 27.6 ng/mL) and the times to peak concentrations ranged from 1.0 to 3.0 hours (mean 2.2 hours). Plasma elimination half-life ranged from 13.0 to 104.9 hours (mean 34.2 hours). The steady state plasma concentrations for a 40 mg q.i.d. regimen have not been established.

INDICATIONS AND USAGE

Megestrol acetate tablets are indicated for the palliative treatment of advanced carcinoma of the breast or endometrium (ie, recurrent, inoperable, or metastatic disease). It should not be used in lieu of currently accepted procedures such as surgery, radiation, or chemotherapy.

CONTRAINDICATIONS

History of hypersensitivity to megestrol acetate or any component of the formulation.

WARNINGS

Megestrol acetate may cause fetal harm when administered to a pregnant woman. Fertility and reproduction studies with high doses of megestrol acetate have shown a reversible feminizing effect on some male rat fetuses. There are no adequate and well-controlled studies in pregnant women. If this drug is used during pregnancy, or if the patient becomes pregnant while taking (receiving) this drug, the patient should be apprised of the potential hazard to the fetus. Women of childbearing potential should be advised to avoid becoming pregnant.

The use of megestrol in other types of neoplastic disease is not recommended.

(See also PRECAUTIONS, Carcinogenesis, Mutagenesis, Impairment of Fertility section.)

The glucocorticoid activity of megestrol acetate tablets has not been fully evaluated. Clinical cases of new onset diabetes mellitus, exacerbation of pre-existing diabetes mellitus, and overt Cushing's syndrome have been reported in association with the chronic use of megestrol acetate. In addition, clinical cases of adrenal insufficiency have been observed in patients receiving or being withdrawn from chronic megestrol acetate therapy in the stressed and non-stressed state. Furthermore, adrenocorticotropin (ACTH) stimulation testing has revealed the frequent occurrence of asymptomatic pituitary-adrenal suppression in patients treated with chronic megestrol acetate therapy. Therefore, the possibility of adrenal insufficiency should be considered in any patient receiving or being withdrawn from chronic megestrol acetate therapy who presents with symptoms and/or signs suggestive of hypoadrenalism (e.g., hypotension, nausea, vomiting, dizziness, or weakness) in either the stressed or non-stressed state. Laboratory evaluation for adrenal insufficiency and consideration of replacement or stress doses of a rapidly acting glucocorticoid are strongly recommended in such patients. Failure to recognize inhibition of the hypothalamic-pituitary-adrenal axis may result in death. Finally, in patients who are receiving or being withdrawn from chronic megestrol acetate therapy, consideration should be given to the use of empiric therapy with stress doses of a rapidly acting glucocorticoid in conditions of stress or serious intercurrent illness. (e.g., surgery, infection).

PRECAUTIONS

General

Close surveillance is indicated for any patient treated for recurrent or metastatic cancer. Use with caution in patients with a history of thromboembolic disease.

Use in Diabetics

Exacerbation of pre-existing diabetes with increased insulin requirements has been reported in association with the use of megestrol.

Information for Patients

Patients using megestrol acetate should receive the following instructions:

1. This medication is to be used as directed by the physician.
2. Report any adverse reaction experiences while taking this medication.

Laboratory Tests

Breast malignancies in which estrogen and/or progesterone receptors are positive are more likely to respond to megestrol.

Carcinogenesis, Mutagenesis, Impairment of Fertility

Administration of megestrol acetate to female dogs for up to 7 years is associated with an increased incidence of both benign and malignant tumors of the breast. Comparable studies in rats and studies in monkeys are not associated with an increased incidence of tumors. The relationship of the dog tumors to humans is unknown but should be considered in assessing the benefit-to-risk ratio when prescribing megestrol acetate and in surveillance of patients on therapy. (See WARNINGS section.)

Pregnancy

Pregnancy Category D. (See WARNINGS section.)

Nursing Mothers

Because of the potential for adverse effects on the newborn, nursing should be discontinued if megestrol is required for treatment of cancer.

Pediatric Use

Safety and effectiveness in pediatric patients have not been established.

Geriatric Use

Insufficient data from clinical studies of megestrol acetate tablets are available for patients 65 years of age and older to determine whether they respond differently than younger patients. Other reported clinical experience has not identified differences in responses between elderly and younger patients. In general, dose selection for an elderly patient should be cautious, usually starting at the low end of the dosing range, reflecting the greater frequency of decreased hepatic, renal, or cardiac function, and of concomitant disease or other drug therapy.

Megestrol acetate is known to be substantially excreted by the kidney, and the risk of toxic reactions to this drug may be greater in patients with impaired renal function. Because elderly patients are more likely to have decreased renal function, care should be taken in dose selection, and it may be useful to monitor renal function.

ADVERSE REACTIONS

Weight Gain

Weight gain is a frequent side effect of megestrol. This gain has been associated with increased appetite and is not necessarily associated with fluid retention.

Thromboembolic Phenomena

Thromboembolic phenomena including thrombophlebitis and pulmonary embolism (in some cases fatal) have been reported.

Glucocorticoid Effects

(See WARNINGS section.)

Other Adverse Reactions

Heart failure, nausea and vomiting, edema, breakthrough menstrual bleeding, dyspnea, tumor flare (with or without hypercalcemia), hyperglycemia, glucose intolerance, alopecia, hypertension, carpal tunnel syndrome, mood changes, hot flashes, malaise, asthenia, lethargy, sweating and rash.

To report SUSPECTED ADVERSE REACTIONS, contact Strides Pharma Inc. at 1-877-244-9825 or go to www.strides.com or FDA at 1-800-FDA-1088 or www.fda.gov/medwatch.

OVERDOSAGE

No serious unexpected side effects have resulted from studies involving megestrol acetate administered in dosages as high as 1600 mg/day. Oral administration of large, single doses of megestrol acetate (5 g/kg) did not produce toxic effects in mice. Megestrol acetate has not been tested for dialyzability; however, due to its low solubility it is postulated that this would not be an effective means of treating overdose.

DOSAGE AND ADMINISTRATION

Breast cancer: 160 mg/day (40 mg q.i.d.).

Endometrial carcinoma: 40 to 320 mg/day in divided doses.

At least 2 months of continuous treatment is considered an adequate period for determining the efficacy of megestrol acetate.

HOW SUPPLIED

Megestrol acetate tablets, 40 mg, are white, round, flat-faced, beveled-edged, bisected, debossed with "Par 290" on one side. They are supplied

Cartons of 100 tablets (10 tablets each blister pack x 10), NDC 0904-7236-61

WARNING: This Unit Dose package is not child resistant and is Intended for Institutional Use Only. Keep this and all drugs out of the reach of children.

STORAGE

Store at 25°C (77°F); excursions permitted to 15° to 30°C (59° to 86°F) [see USP Controlled Room Temperature]. Protect from temperatures above 40^0C (104^0F).

SPECIAL HANDLING

Health Hazard Data

There is no threshold limit value established by OSHA, NIOSH, or ACGIH.

Exposure or "overdose" at levels approaching recommended dosing levels could result in side effects described above (see WARNINGS and ADVERSE REACTIONS). Women at risk of pregnancy should avoid such exposure.

Distributed by:

Strides Pharma Inc.

East Brunswick, NJ 08816

Packaged and Distributed by:

MAJOR® PHARMACEUTICALS

Indianapolis, IN 46268 USA

Refer to package label for Distributor's NDC Number

Revised: 10/21

Package/Label Display Panel

MAJOR®

NDC 0904-7236-61

Unit Dose

MEGESTROL ACETATE

TABLETS, USP

40 mg

Rx only

100 TABLETS